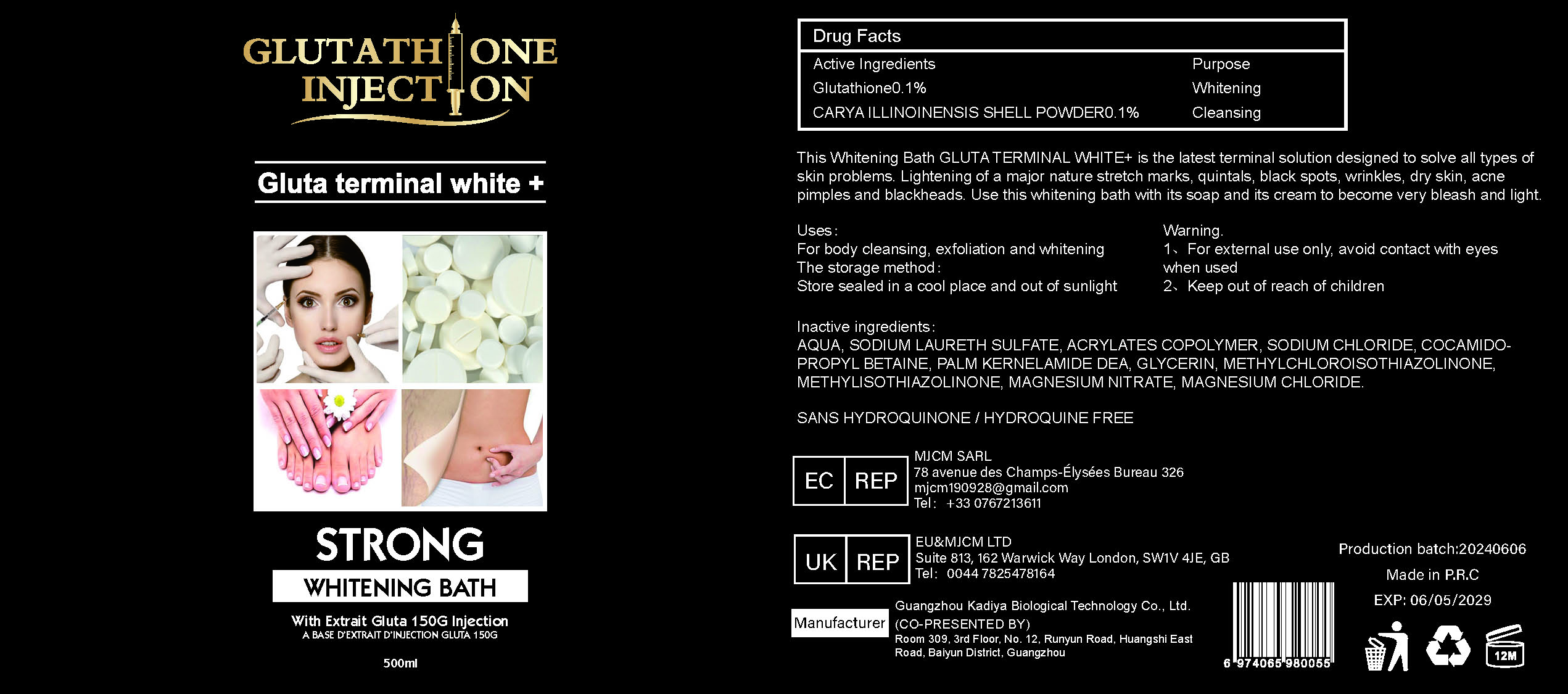 DRUG LABEL: STRONG WHITENING BATH
NDC: 84423-008 | Form: EMULSION
Manufacturer: Guangzhou Kadiya Biotechnology Co., Ltd.
Category: otc | Type: HUMAN OTC DRUG LABEL
Date: 20240626

ACTIVE INGREDIENTS: GLUTATHIONE 0.5 mg/500 mg; CARYA ILLINOINENSIS SHELL 0.5 mg/500 mg
INACTIVE INGREDIENTS: WATER; MAGNESIUM CHLORIDE; METHYLCHLOROISOTHIAZOLINONE; SODIUM LAURETH-2 SULFATE; GLYCERIN; METHYLISOTHIAZOLINONE; MAGNESIUM NITRATE; SODIUM CHLORIDE; COCO/OLEAMIDOPROPYL BETAINE

Purpose section

For body cleansing, exfoliation and whitening

Inactive ingredients

AQUA、SODIUM LAURETH SULFATE、SODIUM CHLORIDE、COCAMIDOPROPYL BETAINE、GLYCERIN、METHYLISOTHIAZOLINONE、MAGNESIUM NITRATE、MAGNESIUM CHLORIDE

Warning

1、For external use only, avoid contact with eyes when used
2、Keep out of reach of children

USAGE

This Whitening Bath GLUTA TERMINAL WHITE+ is the latest terminal solution designed to solve all types of
skin problems. Lightening of a major nature stretch marks, quintals, black spots, wrinkles, dry skin, acne
pimples and blackheads. Use this whitening bath with its soap and its cream to become very bleash and light.

DOSAGE

This Whitening Bath GLUTA TERMINAL WHITE+ is the latest terminal solution designed to solve all types of
skin problems. Lightening of a major nature stretch marks, quintals, black spots, wrinkles, dry skin, acne
pimples and blackheads. Use this whitening bath with its soap and its cream to become very bleash and light.

WARNING

KEEP OUT OF REACH OF CHILDREN SECTION

PACKAGE LABEL

Active Ingredients
Glutathione0.1%
CARYA ILLINOINENSIS SHELL POWDER0.1%

Uses：
For body cleansing, exfoliation and whitening
The storage method：
Store sealed in a cool place and out of sunlight

Warning.
1，For external use only, avoid contact with eyes when used
2，Keep out of reach of children

Inactive ingredients：
AQUA，SODIUM LAURETH SULFATE，SODIUM CHLORIDE，COCAMIDOPROPYL BETAINE，GLYCERIN， METHYLISOTHIAZOLINONE，MAGNESIUM NITRATE，MAGNESIUM CHLORIDE